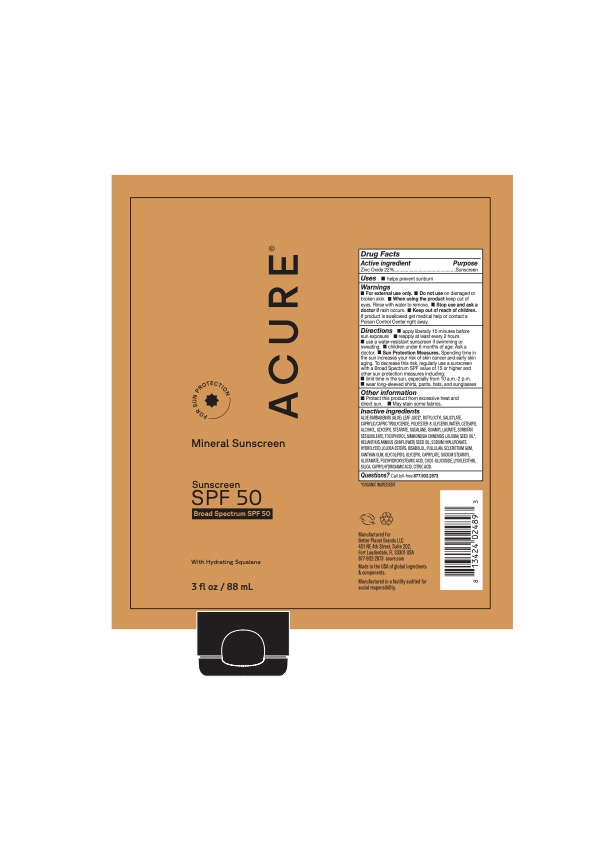 DRUG LABEL: Mineral Sunscreen SPF 50
NDC: 54136-351 | Form: CREAM
Manufacturer: Better Planet Brands LLC
Category: otc | Type: HUMAN OTC DRUG LABEL
Date: 20251203

ACTIVE INGREDIENTS: ZINC OXIDE 22 g/100 g
INACTIVE INGREDIENTS: GLYCERIN; BETASIZOFIRAN; ACENEURAMIC ACID; ANHYDROUS CITRIC ACID; XANTHAN GUM; MEDIUM-CHAIN TRIGLYCERIDES; CETOSTEARYL ALCOHOL; SORBITAN SESQUIOLEATE; SUNFLOWER OIL; HYALURONATE SODIUM; LEVOMENOL; GLYCERYL STEARATE SE; ISOAMYL LAURATE; GLYCERYL CAPRYLATE; LYSOPHOSPHATIDYLCHOLINE, SOYBEAN; ALOE VERA LEAF; .ALPHA.-TOCOPHEROL ACETATE, D-; POLYHYDROXYSTEARIC ACID (2300 MW); POLYESTER-8 (1400 MW, CYANODIPHENYLPROPENOYL CAPPED); WATER; HYDROLYZED JOJOBA ESTERS (ACID FORM); PULLULAN; SODIUM STEAROYL GLUTAMATE; COCO-GLUCOSIDE; CAPRYLHYDROXAMIC ACID; SQUALANE; JOJOBA OIL; BUTYLOCTYL SALICYLATE; SILICON DIOXIDE

Mineral Sunscreen SPF 50

Active ingredients

Zinc Oxide 22%

Purpose

Sunscreen

Uses

• helps prevent sunburn

Warnings

• For external use

• Do not use on damaged or broken skin.

WHEN USING

• When using the product keep out of eyes. Rinse with water to remove.

• Stop use and ask a doctor if rash occurs.

• Keep out of reach of children.

If product is swallowed get medical help or contact a Poison Control Center right away.

Directions

Directions_• apply liberally 15 minutes before sun exposure

reapply at least every 2 hours
use a water-resistant sunscreen if swimming or sweating. • Sun Protection Measures. Spending time in the sun increases your risk of skin cancer and early skin aging. To decrease this risk, regularly use a sunscreen with a Broad Spectrum SPF value of 15 or higher and other sun protection measures including:
limit time in the sun, especially from 10 a.m.-2 p.m.
wear long-sleeved shirts, pants, hats, and sunglasses

Other information

Protect this product from excessive heat and direct sun.
May stain some

Inactive Ingredients

ALOE BARBADENSIS LEAF JUICE*, BUTYLOCTYL SALICYLATE, CAPRYLIC/CAPRIC TRIGLYCERIDE, POLYESTER-8, GLYCERIN, WATER, CETEARYL ALCOHOL, GLYCERYL STEARATE, SQUALANE, ISOAMYL LAURATE, SORBITAN SESQUIOLEATE, TOCOPHEROL, SIMMONDSIA CHINENSIS (JOJOBA) SEED OIL*, HELANTHUS ANNUUS (SUNFLOWER) SEED OIL, SODIUM HYALURONATE, HYDROLYZED JOJOBA ESTERS, BISABOLOL, PULLULAN, SCLEROTIUM GUM, XANTHAN GUM, GLYCOLIPIDS, GLYCERYL CAPRYLATE, SODIUM STEAROYL GLUTAMATE, POLYHYDROXYSTEARIC ACID, COCO-GLUCOSIDE, LYSOLECITHIN, SILICA, CAPRYLHYDROXAMIC ACID, CITRIC ACID

Questions?

Call toll-free 877.902.2873